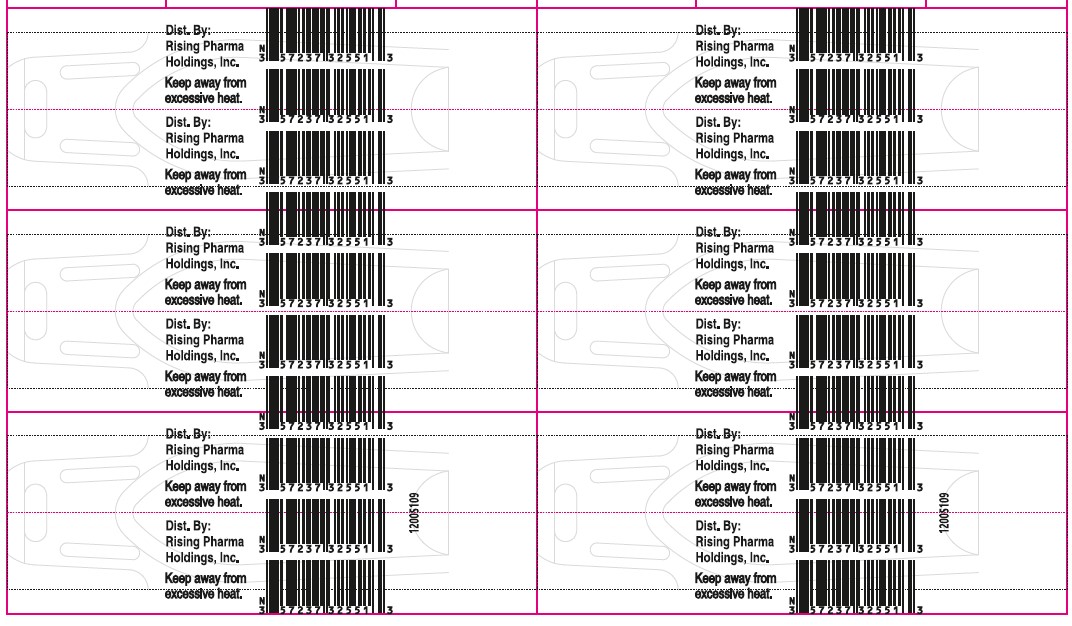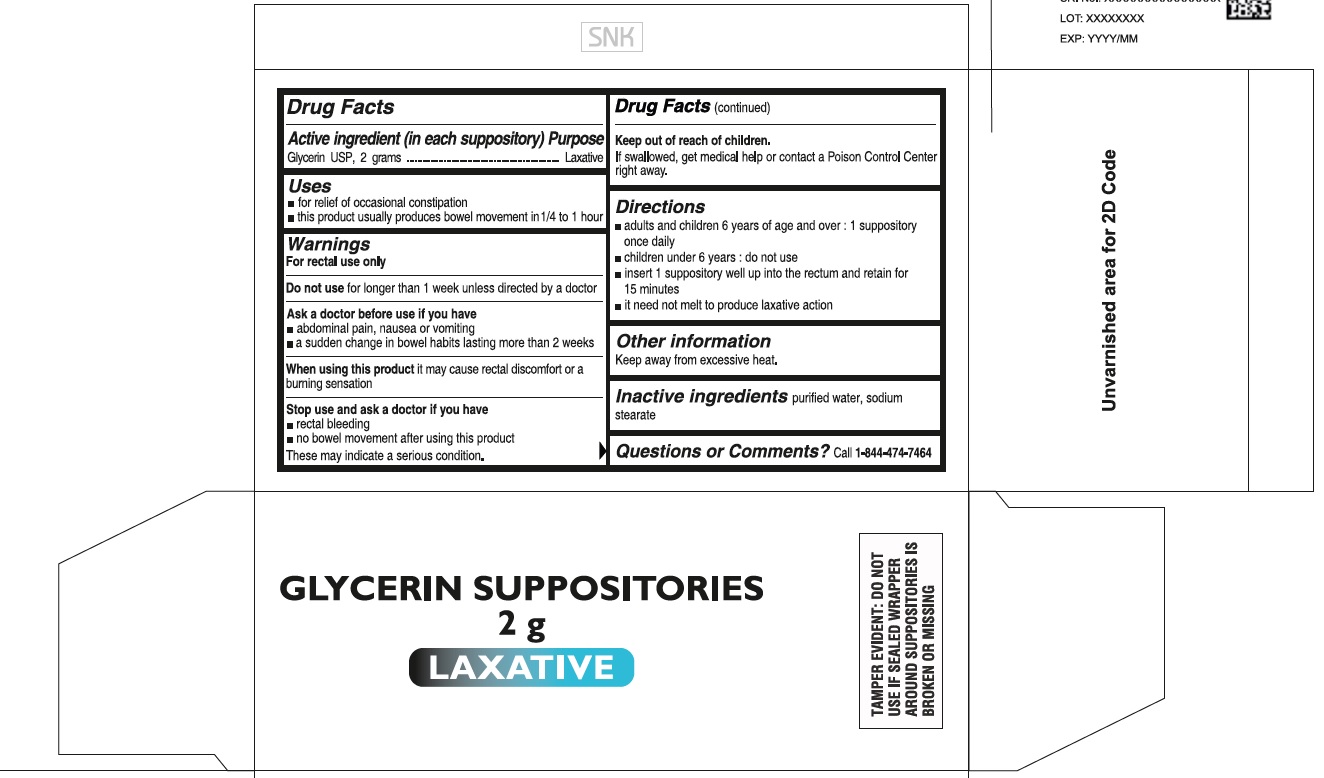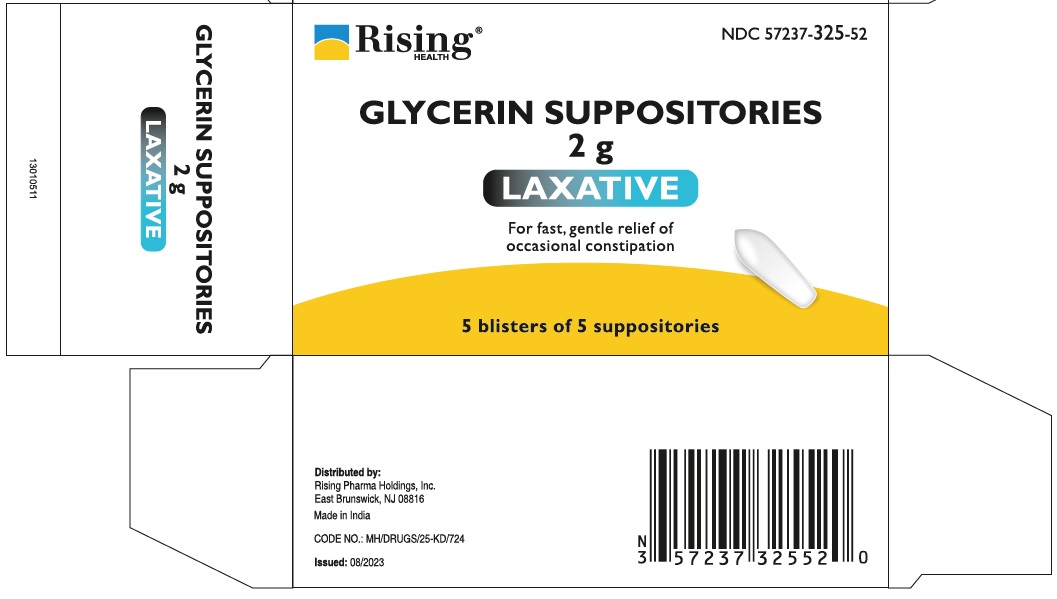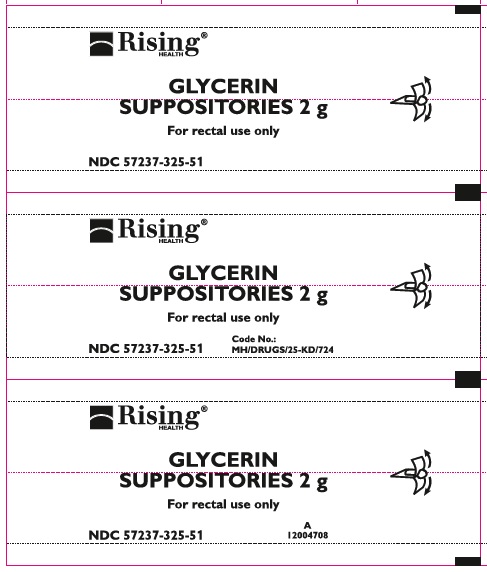 DRUG LABEL: Glycerin
NDC: 57237-325 | Form: SUPPOSITORY
Manufacturer: Rising Pharma Holdings, Inc.
Category: otc | Type: HUMAN OTC DRUG LABEL
Date: 20250908

ACTIVE INGREDIENTS: GLYCERIN 2 g/1 1
INACTIVE INGREDIENTS: WATER; SODIUM STEARATE

Glycerin Suppositories 2 g

Drug Facts

Active ingredient (in each suppository)

Glycerin USP, 2 grams

Purpose

Laxative

Uses

- for relief of occasional constipation
- this product usually produces bowel movement in 1/4 to 1 hour

Warnings

For rectal use only

Do not use for longer than 1 week unless directed by a doctor

Ask a doctor before use if you have

- abdominal pain, nausea or vomiting
- a sudden change in bowel habits lasting more than 2 weeks

When using this product it may cause rectal discomfort or a burning sensation

Stop use and ask a doctor if you have

- rectal bleeding
- no bowel movement after using this product

These may indicate a serious condition.

Keep out of reach of children.

If swallowed, get medical help or contact a Poison Control Center right away.

Directions

- adults and children 6 years of age and over : 1 suppository once daily
- children under 6 years : do not use
- insert 1 suppository well up into rectum and retain for 15 minutes
- it need not melt to produce laxative action

Other information

keep away from excessive heat.

Inactive ingredients

purified water, sodium stearate

Questions or Comments?

Call 1-844-474-7464

TAMPER EVIDENT: DO NOT USE IF SEALED WRAPPER AROUND SUPPOSITORIES IS BROKEN OR MISSING

Distributed by:
Rising Pharma Holdings, Inc.
East Brunswick, NJ 08816

Made in India

CODE NO.: MH/DRUGS/25-KD/724

Issued: 08/2023

PACKAGE LABEL

NDC 57237-325-52 (5 blisters of 5 suppositories)

GLYCERIN SUPPOSITORIES 2 g

LAXATIVE

For fast, gentle relief of occasional constipation

NDC 57237-325-51 (5 suppositories in 1 blister pack)

Front Foil

Back Foil